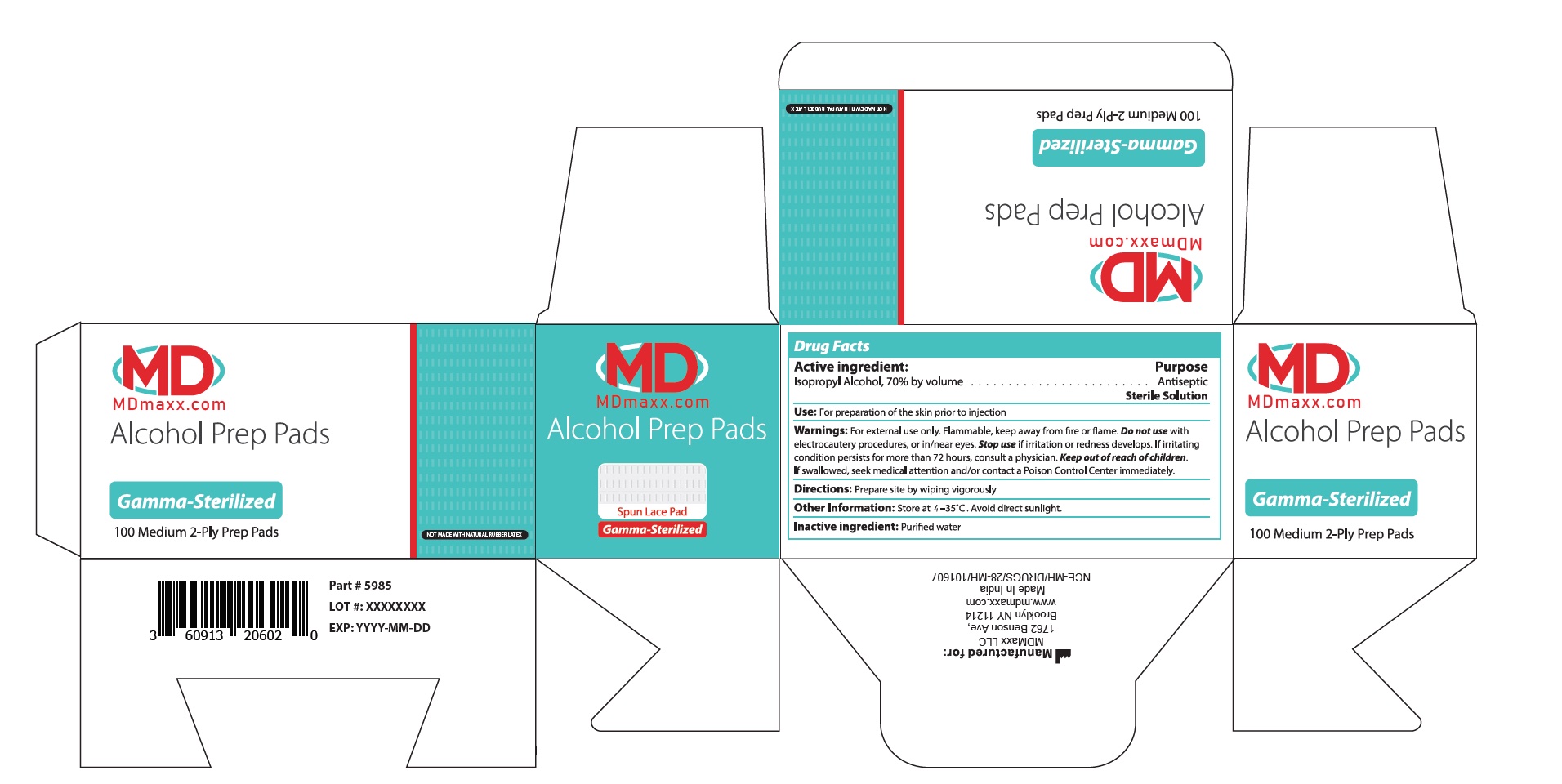 DRUG LABEL: Alcohol Prep Pads
NDC: 60913-206 | Form: SWAB
Manufacturer: Phoenix Healthcare Solutions LLC
Category: otc | Type: HUMAN OTC DRUG LABEL
Date: 20251023

ACTIVE INGREDIENTS: ISOPROPYL ALCOHOL 70 mL/100 mL
INACTIVE INGREDIENTS: WATER

MDMaxx APP 100 Count

ACTIVE INGREDIENT

Isopropyl Alcohol 70% by volume

PURPOSE

Antiseptic

INDICATIONS AND USAGE

For preparation of the skin prior to injection

WARNINGS

For external use only. Flammable, keep away from fire or flame.

Do not use with electocautery procedures, or in/near eyes.

Stop use if irritation or redness develops. If irritating condition persists for more than 72 hours, consult a physician.

KEEP OUT OF REACH OF CHILDREN

If swallowed, seek medical attention and/or contact a Poison Control Center immediately.

DOSAGE AND ADMINISTRATION

Prepare site by wiping vigorously.

STORAGE AND HANDLING

Store at 4-35C. Avoid direct sunlight.

INACTIVE INGREDIENT

Purified water